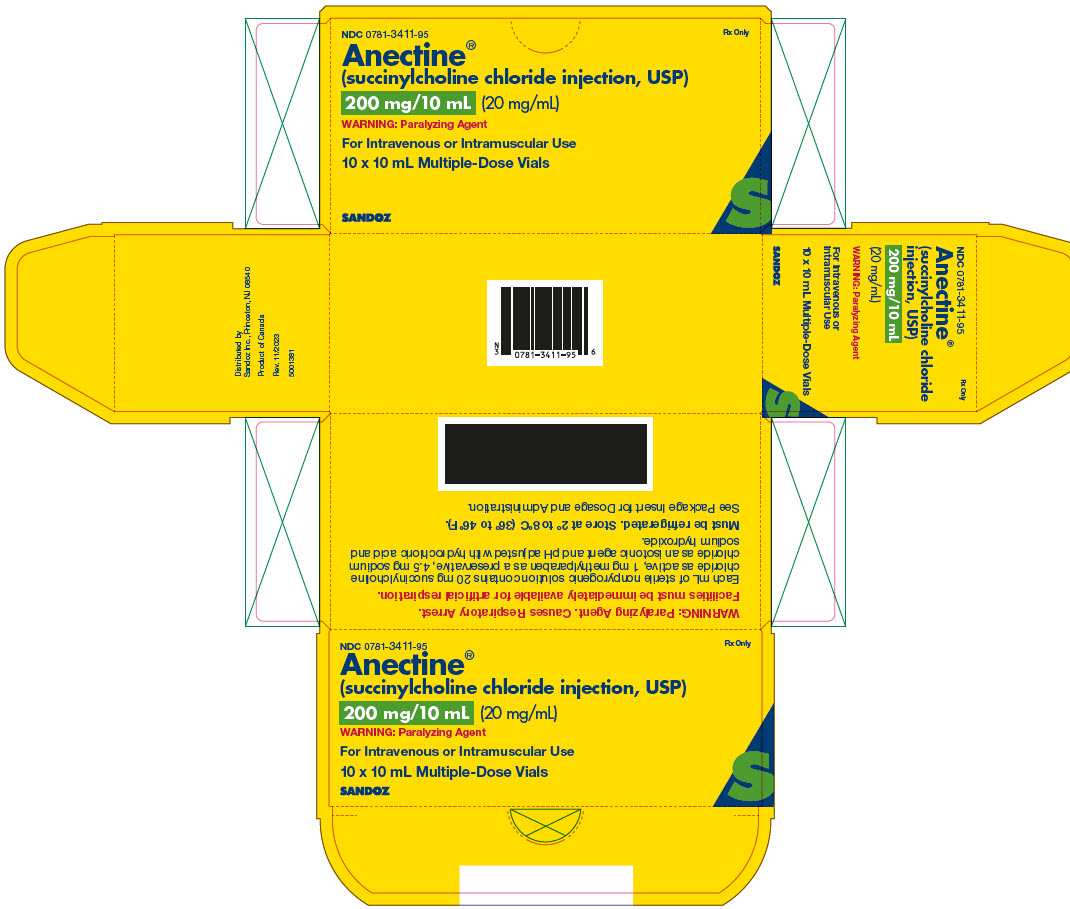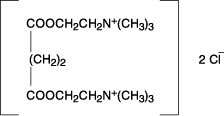 DRUG LABEL: Anectine
NDC: 0781-3411 | Form: INJECTION, SOLUTION
Manufacturer: Sandoz Inc
Category: prescription | Type: HUMAN PRESCRIPTION DRUG LABEL
Date: 20231129

ACTIVE INGREDIENTS: SUCCINYLCHOLINE CHLORIDE 20 mg/1 mL
INACTIVE INGREDIENTS: SODIUM CHLORIDE; HYDROCHLORIC ACID; METHYLPARABEN 1 mg/1 mL; SODIUM HYDROXIDE

HIGHLIGHTS OF PRESCRIBING INFORMATION

These highlights do not include all the information needed to use ANECTINE safely and effectively. See full prescribing information for ANECTINE.
ANECTINE® (succinylcholine chloride) injection, for intravenous or intramuscular use
Initial U.S. Approval: 1952

RECENT MAJOR CHANGES

Contraindications (4) 11/2023
Warnings and Precautions (5.5) 11/2023

WARNING: RISK OF VENTRICULAR DYSRHYTHMIAS, CARDIAC ARREST AND DEATH FROM HYPERKALEMIC RHABDOMYOLYSIS IN PEDIATRIC PATIENTS

See full prescribing information for complete boxed warning.

- Acute rhabdomyolysis with hyperkalemia followed by ventricular dysrhythmias, cardiac arrest, and death has occurred after the administration of succinylcholine to apparently healthy pediatric patients who were subsequently found to have undiagnosed skeletal muscle myopathy, most frequently Duchenne muscular dystrophy. (5.1).
- When a healthy appearing pediatric patient develops cardiac arrest within minutes after administration of ANECTINE not felt to be due to inadequate ventilation, oxygenation, or anesthetic overdose, immediate treatment for hyperkalemia should be instituted. In the presence of signs of malignant hyperthermia, appropriate treatment should be instituted concurrently (5.1).
- Reserve use of ANECTINE in pediatric patients should be for emergency intubation or instances where immediate securing of the airway is necessary, e.g., laryngospasm, difficult airway, full stomach, or for intramuscular use when a suitable vein is inaccessible (5.1).

1 INDICATIONS AND USAGE

ANECTINE is a depolarizing neuromuscular blocker indicated in adults and pediatric patients:

- as an adjunct to general anesthesia (1)
- to facilitate tracheal intubation (1)
- to provide skeletal muscle relaxation during surgery or mechanical ventilation (1).

2 DOSAGE AND ADMINISTRATION

- For intravenous or intramuscular use only (2.1).
- Individualize dosage after careful assessment of the patient (2.1)
- Accidental administration of neuromuscular blocking agents may be fatal. Store ANECTINE with the cap and ferrule intact and in a manner that minimizes the possibility of selecting the wrong product (2.1).
- See full prescribing information for ANECTINE dosage recommendations, preparation instructions, and administration information (2.2, 2.3, 2.4, 2.5).

3 DOSAGE FORMS AND STRENGTHS

Injection: 200 mg/ 10 mL (20 mg/mL) in multiple-dose vials (3)

4 CONTRAINDICATIONS

- Skeletal muscle myopathies (4)
- Known hypersensitivity to succinylcholine (4)
- After the acute phase of injury following major burns, multiple trauma, extensive denervation of skeletal muscle, or upper motor neuron injury (4)
- Known or suspected genetic susceptibility to malignant hyperthermia (4)

5 WARNINGS AND PRECAUTIONS

- Anaphylaxis: Severe anaphylactic reactions to neuromuscular blocking agents, including succinylcholine, have been reported. Some cases have been life-threatening and fatal. Take necessary precautions, such as the immediate availability of appropriate emergency treatment (5.2).
- Risk of Death due to Medication Errors: Unintended administration of ANECTINE results in paralysis, which may lead to respiratory arrest and death. Confirm proper selection of intended product and avoid confusion with other injectable solutions that are present in critical care and other clinical settings (5.3).
- Hyperkalemia: ANECTINE may induce serious cardiac arrhythmias or cardiac arrest due to hyperkalemia (5.4).
- Malignant Hyperthermia: Malignant hyperthermia may occur, especially in individuals with known or suspected susceptibility based on genetic factors or family history. Discontinue triggering agents, administer intravenous dantrolene sodium, and apply supportive therapies (5.5).
- Bradycardia: Intravenous bolus administration may result in profound bradycardia which may progress to asystole is higher following a second dose of succinylcholine. Pretreatment with anticholinergic agents (e.g., atropine) may reduce the occurrence of bradyarrhythmias (5.6).

6 ADVERSE REACTIONS

Adverse reactions reported with succinylcholine are cardiac arrest, malignant hyperthermia, arrhythmias, bradycardia, tachycardia, hypertension, hypotension, hyperkalemia, prolonged respiratory depression or apnea (6).

To report SUSPECTED ADVERSE REACTIONS, contact Sandoz Inc. at 1-800-525-8747 or FDA at 1-800-FDA-1088 or www.fda.gov/medwatch.

7 DRUG INTERACTIONS

Drugs that may Enhance the Neuromuscular Blocking Action of Succinylcholine: promazine, oxytocin, aprotinin, certain non-penicillin antibiotics, quinidine, β-adrenergic blockers, procainamide, lidocaine, trimethaphan, lithium carbonate, magnesium salts, quinine, chloroquine, isoflurane, desflurane, metoclopramide, terbutaline, and drugs that reduce plasma cholinesterase activity. (7.1)

FULL PRESCRIBING INFORMATION

WARNING: RISK OF VENTRICULAR DYSRHYTHMIAS, CARDIAC ARREST AND DEATH FROM HYPERKALEMIC RHABDOMYOLYSIS IN PEDIATRIC PATIENTS

- Acute rhabdomyolysis with hyperkalemia followed by ventricular dysrhythmias, cardiac arrest, and death has occurred after the administration of succinylcholine to apparently healthy pediatric patients who were subsequently found to have undiagnosed skeletal muscle myopathy, most frequently Duchenne muscular dystrophy [see Warnings and Precautions (5.1)].
- When a healthy appearing pediatric patient develops cardiac arrest within minutes after administration of ANECTINE not felt to be due to inadequate ventilation, oxygenation, or anesthetic overdose, immediate treatment for hyperkalemia should be instituted. In the presence of signs of malignant hyperthermia, appropriate treatment should be instituted concurrently [see Warnings and Precautions (5.1)].
- Reserve the use of ANECTINE in pediatric patients for emergency intubation or instances where immediate securing of the airway is necessary, e.g., laryngospasm, difficult airway, full stomach, or for intramuscular use when a suitable vein is inaccessible [see Warnings and Precautions (5.1)].

1 INDICATIONS AND USAGE

ANECTINE is indicated in adults and pediatric patients:

- as an adjunct to general anesthesia
- to facilitate tracheal intubation
- to provide skeletal muscle relaxation during surgery or mechanical ventilation.

2 DOSAGE AND ADMINISTRATION

2.1 Important Dosage and Administration Information

- ANECTINE is for intravenous or intramuscular use only.
- ANECTINE must be titrated to effect by or under supervision of experienced clinicians who are familiar with its actions and with appropriate neuromuscular monitoring techniques.
- ANECTINE should be administered only by those skilled in the management of artificial respiration and only when facilities are instantly available for tracheal intubation and for providing adequate ventilation of the patient, including the administration of oxygen under positive pressure and the elimination of carbon dioxide. The clinician must be prepared to assist or control respiration.
- The dosage of ANECTINE should be individualized and should always be determined by the clinician after careful assessment of the patient.
- To avoid distress to the patient, succinylcholine should not be administered before unconsciousness has been induced. In emergency situations, however, it may be necessary to administer succinylcholine before unconsciousness is induced.
- The occurrence of bradyarrhythmias with administration of ANECTINE may be reduced by pretreatment with anticholinergics (e.g., atropine) [see Warnings and Precautions (5.6)].
- Monitor neuromuscular function with a peripheral nerve stimulator when using ANECTINE by infusion [see Dosage and Administration (2.2)].
- Visually inspect ANECTINE for particulate matter and discoloration prior to administration, whenever solution and container permit. Do not administer solutions which are not clear and colorless.

Risk of Medication Errors

Accidental administration of neuromuscular blocking agents may be fatal. Store ANECTINE with the cap and ferrule intact and in a manner that minimizes the possibility of selecting the wrong product [see Warnings and Precautions (5.3)].

2.2 Dosage Recommendations for Intravenous Use in Adults

For Short Surgical Procedures

The average dose required to produce neuromuscular blockade and to facilitate tracheal intubation is 0.6 mg/kg ANECTINE given intravenously. The optimum intravenous dose will vary among patients and may be from 0.3 to 1.1 mg/kg for adults. Following intravenous administration of doses in this range, neuromuscular blockade develops in about 1 minute; maximum blockade may persist for about 2 minutes, after which recovery takes place within 4 to 6 minutes. Depending on the dose and duration of succinylcholine administration, the characteristic depolarizing neuromuscular block (Phase I block) may change to a block with characteristics superficially resembling a non-depolarizing block (Phase II block) [see Prolonged Neuromuscular Block due to Phase II Block and Tachyphylaxis (5.8), Overdose (10), and Pharmacodynamics (12.2)]. A 5 to 10 mg test dose may be used to determine the sensitivity of the patient and the individual recovery time [see Warnings and Precautions (5.9)].

For Long Surgical Procedures

Continuous Intravenous Infusion

The dose of ANECTINE administered by intravenous infusion depends upon the duration of the surgical procedure and the need for muscle relaxation. The average rate for an adult range between 2.5 and 4.3 mg per minute.

Diluted ANECTINE solutions containing from 1 to 2 mg/mL succinylcholine have commonly been used for continuous infusion [see Dosage and Administration (2.4)]. The more dilute solution (1 mg/mL) is probably preferable from the standpoint of ease of control of the rate of administration of ANECTINE and hence, of relaxation. This diluted ANECTINE solution containing 1 mg/mL of succinylcholine may be administered at a rate of 0.5 mg (0.5 mL) to 10 mg (10 mL) per minute to obtain the required amount of relaxation. The amount required per minute will depend upon the individual response as well as the degree of relaxation require. Monitor neuromuscular function with a peripheral nerve stimulator when using ANECTINE by infusion in order to avoid overdose, detect development of Phase II block, follow its rate of recovery, and assess the effects of reversing agents [see Warnings and Precautions (5.8)].

Intermittent Intravenous Injection

Intermittent intravenous injections of ANECTINE may also be used to provide muscle relaxation for long procedures. An intravenous injection of 0.3 to 1.1 mg/kg may be given initially, followed, at appropriate intervals, by further intravenous injections of 0.04 to 0.07 mg/kg to maintain the degree of relaxation required.

2.3 Dosage Recommendations for Intravenous Use in Pediatric Patients

For emergency tracheal intubation or in instances where immediate securing of the airway is necessary, the intravenous dose of ANECTINE is 2 mg/kg for infants and other small pediatric patients; for older pediatric patients and adolescents the dose is 1 mg/kg [see Warnings and Precautions (5.1) and Use in Specific Populations (8.4)]. The effective dose of ANECTINE in pediatric patients may be higher than that predicted by body weight dosing alone. For example, the usual adult intravenous dose of 0.6 mg/kg is comparable to a dose of 2 mg/kg to 3 mg/kg in neonates and infants up to 6 months of age and 1 mg/kg to 2 mg/kg in infants up to 2 years of age [see Clinical Pharmacology (12.3)].

2.4 Dosage Recommendations for Intramuscular Use in Adults and Pediatric Patients

If a suitable vein is inaccessible, ANECTINE may be given intramuscularly to infants, older pediatric patients, or adults. A dose of up to 3 to 4 mg/kg may be given, but not more than 150 mg total dose should be administered by this route. The onset of effect of succinylcholine given intramuscularly is usually observed in about 2 to 3 minutes.

2.5 Drug Preparation

ANECTINE is supplied in a multi-dose vial and does not require dilution for intravenous or intramuscular bolus dosing.

ANECTINE may be diluted for continuous intravenous infusion to 1 mg/mL or 2 mg/mL in a solution such as:

- 5% Dextrose Injection, USP, or
- 0.9% Sodium Chloride Injection, USP

Prepare the diluted ANECTINE solution for single patient use only. Store the diluted ANECTINE solution in a refrigerator [2 °C to 8°C (36 °F to 46 °F)] and use within 24 hours after preparation. Visually inspect the diluted ANECTINE solution for particulate matter and discoloration prior to administration. Do not administer solutions that are not clear and colorless. Discard any unused portion of the diluted ANECTINE solution.

2.6 Drug Incompatibility

ANECTINE is acidic (pH 3.5) and may not be compatible with alkaline solutions having a pH greater than 8.5 (e.g., barbiturate solutions). Therefore, do not mix ANECTINE with alkaline solutions.

3 DOSAGE FORMS AND STRENGTHS

ANECTINE (Succinylcholine Chloride Injection, USP) is supplied as a clear, colorless solution:

- 200 mg/10 mL (20 mg/mL) in multiple-dose vials contains: 20 mg of succinylcholine anhydrous (equivalent to 22.65 mg of Succinylcholine Chloride, USP).

4 CONTRAINDICATIONS

ANECTINE is contraindicated in patients with:

- Known or suspected genetic susceptibility to malignant hyperthermia [see WARNINGS, Malignant Hyperthermia (5.5), CLINICAL PHARMACOLOGY, Pharmacogenomics (12.5)]
- Skeletal muscle myopathies [see WARNINGS, Ventricular Dysrhythmias, Cardiac Arrest, and Death From Hyperkalemic Rhabdomyolysis in Pediatric Patients (5.1)]
- Known hypersensitivity to succinylcholine [see Warnings and Precautions (5.2)]
- After the acute phase of injury following major burns, multiple trauma, extensive denervation of the skeletal muscle, or upper neuron injury because succinylcholine administered to such individuals may result in severe
  hyperkalemia, which may result in cardiac arrest [see Warnings and Precautions (5.4)]

5 WARNINGS AND PRECAUTIONS

5.1 Ventricular Dysrhythmias, Cardiac Arrest and Death from Hyperkalemic Rhabdomyolysis in Pediatric Patients

There have been reports of ventricular dysrhythmias, cardiac arrest, and death secondary to acute rhabdomyolysis with hyperkalemia in apparently healthy pediatric patients who received ANECTINE. Many of these pediatric patients were subsequently diagnosed with a skeletal muscle myopathy, such as Duchenne muscular dystrophy

This syndrome often presents as peaked T-waves and sudden cardiac arrest within minutes after the administration of ANECTINE in healthy appearing pediatric patients (usually, but not exclusively, males, and most frequently 8 years of age or younger). There have also been reports in adolescents.

Therefore, when a healthy appearing infant or child develops cardiac arrest soon after administration of ANECTINE not felt to be due to inadequate ventilation, oxygenation, or anesthetic overdose, immediate treatment for hyperkalemia should be instituted. This should include administration of intravenous calcium, bicarbonate, and glucose with insulin, with hyperventilation. Due to the abrupt onset of this syndrome, routine resuscitative measures are likely to be unsuccessful. However, extraordinary and prolonged resuscitative efforts have resulted in successful resuscitation in some reported cases. In addition, in the presence of signs of malignant hyperthermia, appropriate treatment should be instituted concurrently [see Warnings and Precautions (5.5)].

Since there may be no signs or symptoms to alert the practitioner to which patients are at risk, it is recommended that the use of ANECTINE in pediatric patients should be reserved for emergency intubation or instances where immediate securing of the airway is necessary, e.g., laryngospasm, difficult airway, full stomach, or for intramuscular use when a suitable vein is inaccessible.

5.2 Anaphylaxis

Severe anaphylactic reactions to neuromuscular blocking agents, including ANECTINE, have been reported. These reactions have in some cases been life-threatening and fatal. Due to the potential severity of these reactions, the necessary precautions, such as the immediate availability of appropriate emergency treatment, should be taken. Precautions should also be taken in those individuals who have had previous anaphylactic reactions to other neuromuscular blocking agents since cross-reactivity between neuromuscular blocking agents, both depolarizing and non-depolarizing, has been reported in this class of drugs. Therefore, assess patients for previous anaphylactic reactions to other neuromuscular blocking agents before administering ANECTINE.

5.3 Risk of Death due to Medication Errors

Administration of ANECTINE results in paralysis, which may lead to respiratory arrest and death; this progression may be more likely to occur in a patient for whom ANECTINE use was not intended. Confirm proper selection of intended product and avoid confusion with other injectable solutions that are present in critical care and other clinical settings. If another healthcare provider is administering the product, ensure that the intended dose is clearly labeled and communicated.

5.4 Hyperkalemia

ANECTINE administration may induce serious cardiac arrhythmias or cardiac arrest due to hyperkalemia in patients with electrolyte abnormalities and those who may have digitalis toxicity.

ANECTINE is contraindicated after the acute phase of injury following major burns, multiple trauma, extensive denervation of skeletal muscle, or upper motor neuron injury [see Contraindications (4)]. The risk of hyperkalemia in these patients increases over time and usually peaks at 7 to 10 days after the injury. The risk is dependent on the extent and location of the injury. The precise time of onset and the duration of the risk period are undetermined.

Patients with chronic abdominal infection, subarachnoid hemorrhage, or conditions causing degeneration of central and peripheral nervous systems are at increased risk for developing severe hyperkalemia after ANECTINE administration. Consider avoiding use of ANECTINE in these patients or verify the patient’s baseline potassium levels are within the normal range prior to ANECTINE administration.

5.5 Malignant Hyperthermia

In susceptible individuals, succinylcholine may trigger malignant hyperthermia, a skeletal muscle hypermetabolic state leading to high oxygen demand. Fatal outcomes of malignant hyperthermia have been reported.

The risk of developing malignant hyperthermia increases with the concomitant administration of succinylcholine and volatile anesthetic agents. Anectine can induce malignant hyperthermia in patients with known or suspected susceptibility based on genetic factors or family history, including those with certain inherited ryanodine receptor (RYR1) or dihydropyridine receptor (CACNA1S) variants [see Contraindications (4), Clinical Pharmacology (12.5)].

Signs consistent with malignant hyperthermia may include hyperthermia, hypoxia, hypercapnia, muscle rigidity (e.g., jaw muscle spasm), tachycardia (e.g., particularly that unresponsive to deepening anesthesia or analgesic medication administration), tachypnea, cyanosis, arrhythmias, hypovolemia, and hemodynamic instability. Skin mottling, coagulopathies, and renal failure may occur later in the course of the hypermetabolic process.

Successful treatment of malignant hyperthermia depends on early recognition of the clinical signs. If malignant hyperthermia is suspected, discontinue all triggering agents (i.e., volatile anesthetic agents and succinylcholine), administer intravenous dantrolene sodium, and initiate supportive therapies. Consult prescribing information for intravenous dantrolene sodium for additional information on patient management. Supportive therapies include administration of supplemental oxygen and respiratory support based on clinical need, maintenance of hemodynamic stability and adequate urinary output, management of fluid and electrolyte balance, correction of acid base derangements, and institution of measures to control rising temperature.

5.6 Bradycardia

Intravenous bolus administration of ANECTINE in infants or pediatric patients may result in profound bradycardia or, rarely, asystole. As in adults, the incidence of bradycardia in pediatric patients, is higher following a second dose of succinylcholine. The incidence and severity of bradycardia is higher in pediatric patients than adults. Whereas bradycardia is common in pediatric patients after an initial dose of 1.5 mg/kg, bradycardia is generally seen in adults only after repeated exposure. Pretreatment with anticholinergic agents (e.g., atropine) may reduce the occurrence of bradyarrhythmias.

5.7 Increase in Intraocular Pressure

Succinylcholine causes an increase in intraocular pressure. Avoid use of ANECTINE in instances in which an increase in intraocular pressure is undesirable (e.g., narrow angle glaucoma, penetrating eye injury) unless the potential benefit of its use outweighs the potential risk.

5.8 Prolonged Non-depolarizing Block due to Phase II block and Tachyphylaxis

When succinylcholine is given over a prolonged period, the characteristic depolarization block of the myoneural junction (Phase I block) may change to a block with characteristics superficially resembling a non-depolarizing block (Phase II block) [see Clinical Pharmacology (12.2)]. Prolonged respiratory muscle paralysis or weakness may be observed in patients manifesting this transition to Phase II block. Tachyphylaxis occurs with repeated administration [see Clinical Pharmacology (12.2)].

When Phase II block is suspected in cases of prolonged neuromuscular blockade, positive diagnosis should be made by peripheral nerve stimulation prior to administration of any anticholinesterase drug. Reversal of Phase II block is a medical decision which must be made upon the basis of the patient, clinical pharmacology, and the experience and judgment of the physician. The presence of Phase II block is indicated by fade of responses to successive stimuli (preferably “train of four”). The use of an anticholinesterase drug to reverse Phase II block should be accompanied by appropriate doses of an anticholinergic drug, such as neostigmine, to prevent disturbances of cardiac rhythm. After adequate reversal of Phase II block with an anticholinesterase agent, the patient should be continually observed for at least 1 hour for signs of return of muscle relaxation. Reversal should not be attempted unless: (1) A peripheral nerve stimulator is used to determine the presence of Phase II block (since anticholinesterase agents will potentiate succinylcholine-induced Phase I block), and (2) Spontaneous recovery of muscle twitch has been observed for at least 20 minutes and has reached a plateau with further recovery proceeding slowly; this delay is to ensure complete hydrolysis of succinylcholine by plasma cholinesterase prior to administration of the anticholinesterase agent. Should the type of block be misdiagnosed, depolarization of the type initially induced by succinylcholine (i.e., Phase I block) will be prolonged by an anticholinesterase agent.

5.9 Risk of Prolonged Neuromuscular Block in Patients with Reduced Plasma Cholinesterase Activity

ANECTINE is not recommended in patients with reduced plasma cholinesterase (pseudocholinesterase) activity. The likelihood of prolonged neuromuscular block following administration of ANECTINE must be considered in such patients [see Dosage and Administration (2.1)].

Plasma cholinesterase activity may be diminished in the presence of genetic abnormalities of plasma cholinesterase (e.g., patients heterozygous or homozygous for atypical plasma cholinesterase gene), pregnancy, severe liver or kidney disease, malignant tumors, infections, burns, anemia, decompensated heart disease, peptic ulcer, or myxedema. Plasma cholinesterase activity may also be diminished by chronic administration of oral contraceptives, glucocorticoids, or certain monoamine oxidase inhibitors, and by irreversible inhibitors of plasma cholinesterase (e.g., organophosphate insecticides, echothiophate, and certain antineoplastic drugs) [see Drug Interactions (7.1)].

Patients homozygous for atypical plasma cholinesterase gene (1 in 2500 patients) are extremely sensitive to the neuromuscular blocking effect of succinylcholine. In these patients, a 5 to 10 mg test dose of ANECTINE may be administered to evaluate sensitivity to succinylcholine, or neuromuscular blockade may be produced by the cautious administration of a 1-mg/mL solution of succinylcholine by slow intravenous infusion. Apnea or prolonged muscle paralysis should be treated with controlled respiration.

5.10 Risk of Additional Trauma in Patients with Fractures or Muscle Spasms

ANECTINE should be employed with caution in patients with fractures or muscle spasm because the initial muscle fasciculations may cause additional trauma. Monitor neuromuscular transmission and the development of fasciculations throughout the use of neuromuscular blocking agents.

5.11 Transient Increase in Intracranial Pressure

ANECTINE may cause a transient increase in intracranial pressure; however, adequate anesthetic induction prior to administration of succinylcholine will minimize this effect.

5.12 Risk of Aspiration due to Increase in Intragastric pressure

ANECTINE may increase intra-gastric pressure, which could result in regurgitation and possible aspiration of stomach contents. Evaluate patients at risk for aspiration and regurgitation. Monitor patients during induction of anesthesia and neuromuscular blockade for clinical signs of vomiting and/or aspiration.

5.13 Prolonged Neuromuscular block in Patients with Hypokalemia or Hypocalcemia

Neuromuscular blockade may be prolonged in patients with hypokalemia (e.g., after severe vomiting, diarrhea, digitalisation and diuretic therapy) or hypocalcemia (e.g., after massive transfusions). Correct severe electrolyte disturbances when possible. In order to help preclude possible prolongation of neuromuscular block, monitor neuromuscular transmission throughout the use of ANECTINE.

5.14 Risks due to Inadequate Anesthesia

Neuromuscular blockade in the conscious patient can lead to distress. Use ANECTINE in the presence of appropriate sedation or general anesthesia. Monitor patients to ensure that the level of anesthesia is adequate. In emergency situations, however, it may be necessary to administer ANECTINE before unconsciousness is induced.

6 ADVERSE REACTIONS

The following clinically significant adverse reactions are discussed in greater detail in other sections of the labeling:

- Ventricular Dysrhythmias, Cardiac Arrest and Death from Hyperkalemic Rhabdomyolysis in Pediatric Patients [see Warnings and Precautions (5.1)]
- Anaphylaxis [see Warnings and Precautions (5.2)]
- Hyperkalemia [see Warnings and Precautions (5.4)]
- Malignant hyperthermia [see Warnings and Precautions (5.5)]
- Bradycardia [see Warnings and Precautions (5.6)]
- Increased intraocular pressure [see Warnings and Precautions (5.7)]
- Prolonged Neuromuscular Block due to Phase II Block and Tachyphylaxis [see Warnings and Precautions (5.8)]

The following adverse reactions associated with the use of succinylcholine were identified in clinical studies or postmarketing reports. Because some of these reactions were reported voluntarily from a population of uncertain size, it is not always possible to reliably estimate their frequency or establish a causal relationship to drug exposure:

Cardiovascular disorders: Cardiac arrest, arrhythmias, bradycardia, tachycardia, hypertension, hypotension

Electrolyte disorders: Hyperkalemia

Eye disorders: Increased intraocular pressure

Gastrointestinal disorders: Excessive salivation

Immune system disorders: Hypersensitivity reactions including anaphylaxis (in some cases life-threatening and fatal)

Musculoskeletal disorders: Malignant hyperthermia, rhabdomyolysis with possible myoglobinuric acute renal failure, muscle fasciculation, jaw rigidity, postoperative muscle pain

Respiratory disorders: Prolonged respiratory depression or apnea

Skin disorders: Rash

7 DRUG INTERACTIONS

7.1 Drugs that May Affect the Neuromuscular Blocking Action of ANECTINE

Drugs that may enhance the neuromuscular blocking action of succinylcholine include: promazine, oxytocin, aprotinin, certain non-penicillin antibiotics, β-adrenergic blockers, procainamide, lidocaine, trimethaphan, lithium carbonate, magnesium salts, quinine, chloroquine, diethylether, isoflurane, desflurane, metoclopramide, and terbutaline.

The neuromuscular blocking effect of succinylcholine may be enhanced by drugs that reduce plasma cholinesterase activity (e.g., chronically administered oral contraceptives, glucocorticoids, or certain monoamine oxidase inhibitors) or by drugs that irreversibly inhibit plasma cholinesterase [see Warnings and Precautions (5.9)].

If other neuromuscular blocking agents are to be used during the same procedure, the possibility of a synergistic or antagonistic effect should be considered.

8 USE IN SPECIFIC POPULATIONS

8.1 Pregnancy

Risk Summary

Available data from published literature from case reports and case series over decades of use with succinylcholine during pregnancy have not identified a drug-associated risk of major birth defects, miscarriage, or adverse maternal or fetal outcomes. Succinylcholine is used commonly during delivery by caesarean section to provide muscle relaxation. If succinylcholine is used during labor and delivery, there is a risk for prolonged apnea in some pregnant women (see Clinical Considerations). Animal reproduction studies have not been conducted with succinylcholine chloride.

The background risk of major birth defects and miscarriage for the indicated population is unknown. All pregnancies have a background risk of birth defect, loss, or other adverse outcomes. In the U.S. general population, the estimated background risk of major birth defects and miscarriage in clinically recognized pregnancies is 2 to 4% and 15 to 20%, respectively.

Clinical Considerations

Maternal Adverse Reactions

Plasma cholinesterase levels are decreased by approximately 24% during pregnancy and for several days postpartum which can prolong the effect of ANECTINE. Therefore, some pregnant or newly postpartum patients may experience prolonged apnea following administration of ANECTINE.

Fetal/Neonatal Adverse Reactions

Apnea and flaccidity may occur in the newborn after repeated high doses to, or in the presence of atypical plasma cholinesterase in the mother.

Labor or Delivery

Succinylcholine is commonly used to provide muscle relaxation during delivery by caesarean section. Succinylcholine is known to cross the placental barrier in an amount that is dependent on the concentration gradient between the maternal and fetal circulation.

8.2 Lactation

Risk Summary

There are no data on the presence of succinylcholine or its metabolite in either human or animal milk, the effects on the breastfed infant, or the effects on milk production. The developmental and health benefits of breastfeeding should be considered along with the mother’s clinical need for ANECTINE and any potential adverse effects on the breastfed infant from ANECTINE or from the underlying maternal condition.

8.4 Pediatric Use

Safety and effectiveness of succinylcholine chloride have been established in pediatric patients age groups, neonate to adolescent. Since there is a risk of ventricular dysrhythmias, cardiac arrest, and death from hyperkalemic rhabdomyolysis in pediatric patients, reserve the use of ANECTINE in pediatric patients for emergency intubation or instances where immediate securing of the airway is necessary, e.g., laryngospasm, difficult airway, full stomach, or for intramuscular use when a suitable vein is inaccessible [see Warnings and Precautions (5.1)].

Intravenous bolus administration of ANECTINE in infants or pediatric patients may result in profound bradycardia or, rarely, asystole. The incidence and severity of bradycardia is higher in pediatric patients than adults [see Warnings and Precautions (5.6)].

The effective dose of ANECTINE in pediatric patients may be higher than that predicted by body weight dosing alone [see Dosage and Administration (2.3)].

8.5 Geriatric Use

Clinical studies of succinylcholine chloride did not include sufficient numbers of subjects aged 65 and over to determine whether they respond differently from younger subjects. Other reported clinical experience has not identified differences in responses between the elderly and younger patients.

In general, dose selection for an elderly patient should be cautious, usually starting at the low end of the dosing range, reflecting the greater frequency of decreased hepatic, renal, or cardiac function, and of concomitant disease or other drug therapy.

10 OVERDOSAGE

Overdosage with ANECTINE may result in neuromuscular block beyond the time needed for surgery and anesthesia. This may be manifested by skeletal muscle weakness, decreased respiratory reserve, low tidal volume, or apnea. The primary treatment is maintenance of a patent airway and respiratory support until recovery of normal respiration is assured. Depending on the dose and duration of ANECTINE administration, the characteristic depolarizing neuromuscular block (Phase I) may change to a block with characteristics superficially resembling a non-depolarizing block (Phase II) [see Warnings and Precautions (5.8)].

11 DESCRIPTION

ANECTINE (Succinylcholine Chloride Injection, USP) is a short-acting depolarizing neuromuscular blocker, for intravenous (IV) or intramuscular administration. Anectine contains succinylcholine chloride as the active pharmaceutical ingredient.

Succinylcholine Chloride, USP is chemically assigned as C14H30Cl2N2O4 with a molecular weight of 361.305 g/mol. Succinylcholine chloride is a white, odorless, slightly bitter powder and very soluble in water. The drug is unstable in alkaline solutions but relatively stable in acid solutions, depending upon the concentration of the solution and the storage temperature. Solutions of succinylcholine chloride should be stored under refrigeration to preserve potency. ANECTINE injection is a sterile nonpyrogenic solution for intravenous injection where each mL contains 20 mg succinylcholine chloride as active, 1 mg methylparaben as a preservative, 4.5 mg sodium chloride as an isotonic agent and pH adjusted to 3.5 with hydrochloric acid and sodium hydroxide.

The chemical name for succinylcholine chloride is 2,2'-[(1,4-dioxo-1,4-butanediyl)bis(oxy)] bis[N,N,N- trimethylethanaminium] dichloride, and the structural formula is:

12 CLINICAL PHARMACOLOGY

12.1 Mechanism of Action

Succinylcholine is a depolarizing neuromuscular blocker. As does acetylcholine, it combines with the cholinergic receptors of the motor end plate to produce depolarization. This depolarization may be observed as fasciculations. Subsequent neuromuscular transmission is inhibited so long as adequate concentration of succinylcholine remains at the receptor site. Onset of flaccid paralysis is rapid (less than one minute after intravenous administration), and with single administration lasts approximately 4 to 6 minutes.

The paralysis following administration of succinylcholine is progressive, with differing sensitivities of different muscles. This initially involves consecutively the levator muscles of the face, muscles of the glottis, and finally, the intercostals and the diaphragm and all other skeletal muscles.

12.2 Pharmacodynamics

Depending on the dose and duration of succinylcholine administration, the characteristic depolarizing neuromuscular block (Phase I block) may change to a block with characteristics superficially resembling a non-depolarizing block (Phase II block). This may be associated with prolonged respiratory muscle paralysis or weakness in patients who manifest the transition to Phase II block. When this diagnosis is confirmed by peripheral nerve stimulation, it may sometimes be reversed with anticholinesterase drugs such as neostigmine [see Warnings and Precautions (5.8)]. The transition from Phase I to Phase II block has been reported in seven of seven patients studied under halothane anesthesia after an accumulated dose of 2 to 4 mg/kg succinylcholine (administered in repeated, divided doses). The onset of Phase II block coincided with the onset of tachyphylaxis and prolongation of spontaneous recovery. In another study, using balanced anesthesia (N2O/O2/narcotic-thiopental) and succinylcholine infusion, the transition was less abrupt, with great individual variability in the dose of succinylcholine required to produce Phase II block. Of 32 patients studied, 24 developed Phase II block. Tachyphylaxis was not associated with the transition to Phase II block, and 50% of the patients who developed Phase II block experienced prolonged recovery.

Anticholinesterase drugs may not always be effective. If given before succinylcholine is metabolized by cholinesterase, anticholinesterase drugs may prolong rather than shorten paralysis.

Succinylcholine has no direct effect on the myocardium. Succinylcholine stimulates both autonomic ganglia and muscarinic receptors which may cause changes in cardiac rhythm, including cardiac arrest. Changes in rhythm, including cardiac arrest, may also result from vagal stimulation, which may occur during surgical procedures, or from hyperkalemia, particularly in pediatric patients [see Warnings and Precautions (5.1, 5.4 and 5.6), Use in Specific Populations (8.4)]. These effects are enhanced by halogenated anesthetics.

Succinylcholine causes an increase in intraocular pressure immediately after its injection and during the fasciculation phase, and slight increases which may persist after onset of complete paralysis [see Warnings and Precautions (5.7)].

Succinylcholine may cause slight increases in intracranial pressure immediately after its injection and during the fasciculation phase [see Warnings and Precautions (5.10)].

As with other neuromuscular blocking agents, the potential for releasing histamine is present following succinylcholine administration. Signs and symptoms of histamine-mediated release such as flushing, hypotension, and bronchoconstriction are, however, uncommon in normal clinical usage.

Succinylcholine has no effect on consciousness, pain threshold, or cerebration. It should be used only with adequate anesthesia.

Succinylcholine has no direct action on the uterus or other smooth muscle structures. Because it is highly ionized and has low fat solubility, it does not readily cross the placenta.

Tachyphylaxis occurs with repeated administration [see Warnings and Precautions (5.8)].

12.3 Pharmacokinetics

Elimination

Metabolism

Succinylcholine is rapidly hydrolyzed by plasma cholinesterase to succinylmonocholine (which possesses clinically insignificant depolarizing muscle relaxant properties) and then more slowly to succinic acid and choline.

Excretion

About 10% of the drug is excreted unchanged in the urine.

Specific Populations

Pediatric Patients

Due to the relatively large volume of distribution in the pediatric patient versus the adult patient, the effective dose of ANECTINE in pediatric patients may be higher than that predicted by body weight dosing alone [see Dosage and Administration (2.3)].

12.5 Pharmacogenomics

RYR1 and CACNA1S are polymorphic genes, and multiple pathogenic variants have been associated with malignant hyperthermia susceptibility (MHS) in patients receiving succinylcholine, including Anectine. Case reports as well as ex-vivo studies have identified multiple variants in RYR1 and CACNA1S associated with MHS. Variant pathogenicity should be assessed based on prior clinical experience, functional studies, prevalence information, or other evidence [see Contraindications (4), Warnings and Precautions (5.5)].

13 NONCLINICAL TOXICOLOGY

13.1 Carcinogenesis, Mutagenesis, Impairment of Fertility

Carcinogenesis

There have been no long-term studies performed in animals to evaluate carcinogenic potential of succinylcholine.

Mutagenesis

Adequate studies have not been completed to evaluate the genotoxic potential of succinylcholine.

Impairment of Fertility

There are no studies to evaluate the potential impact of succinylcholine on fertility.

16 HOW SUPPLIED/STORAGE AND HANDLING

ANECTINE (Succinylcholine Chloride Injection, USP) is supplied as a clear, colorless solution in multiple-dose vials.

200 mg/10 mL (20 mg/mL)

Carton of 10 Vials NDC 0781-3411-95

Store in refrigerator at 2° to 8°C (36° to 46°F).

The multi-dose vials are stable for up to 14 days at room temperature without significant loss of potency.

Distributed by

Sandoz Inc., Princeton, NJ 08540

PACKAGE/LABEL PRINCIPAL DISPLAY PANEL

NDC 0781-3411-95

Anectine®

(succinylcholine chloride injection, USP)

200 mg/10 mL

(20 mg/mL)

WARNING: Paralyzing Agent

For Intravenous or Intramuscular Use

Rx Only

10 x 10 mL Multiple-Dose Vials

SANDOZ